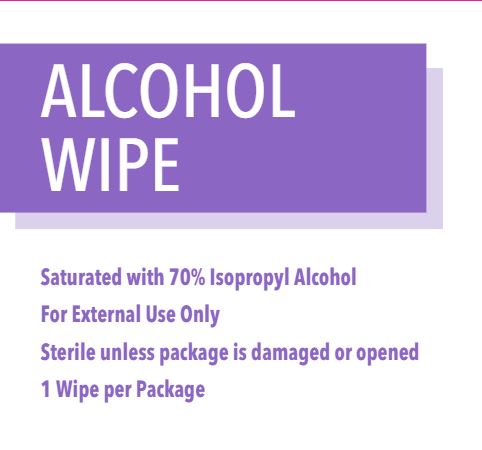 DRUG LABEL: First Aid Direct Alcohol Wipe
NDC: 42961-128 | Form: SPONGE
Manufacturer: Cintas Corporation
Category: otc | Type: HUMAN OTC DRUG LABEL
Date: 20250929

ACTIVE INGREDIENTS: ISOPROPYL ALCOHOL 0.7 mL/1 mL
INACTIVE INGREDIENTS: WATER

First Aid Direct Alcohol Wipe

Active ingredient (in each towelette)

Isopropyl Alcohol 70%

Purpose

Antiseptic cleanser

Uses

for preparation of the skin prior to an injection

Warnings

For external use only.

Flammable, keep away from fire or flame.

Do not use

- with electrocautery procedures
- in the eyes. If contact occurs, flush eyes with water.

Stop use and ask a doctor if irritation and redness develop

Keep out of reach of children. If swallowed, get medical help or contact a Poison Control Center right away.

Directions

wipe injection site vigorously and discard.

Other information

store at room temperature

Inactive ingredients

purified water

Questions?

1-877-973-2811 M-F 8AM-5PM

Principal Display Panel

ALCOHOL WIPE

Saturated with 70% Isopropyl Alcohol

For External Use Only

Sterile unless package is damaged or opened

1 Wipe per Package